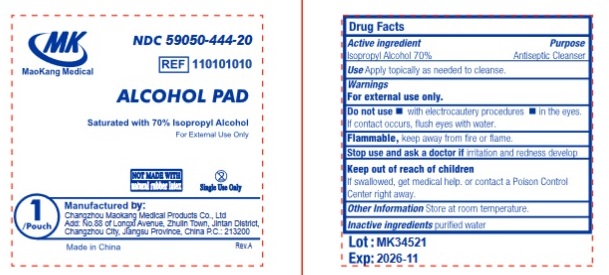 DRUG LABEL: MK Alcohol Prep Pads Medium
NDC: 59050-444 | Form: LIQUID
Manufacturer: Changzhou Maokang Medical Products Co., Ltd
Category: otc | Type: HUMAN OTC DRUG LABEL
Date: 20241121

ACTIVE INGREDIENTS: ISOPROPYL ALCOHOL 70 mL/100 mL
INACTIVE INGREDIENTS: WATER

MK Alcohol Prep Pads Medium Non-Sterile

Active ingredient

Isopropyl Alcohol, 70% v/v

Purpose

Antiseptic

Use

For preparation of skin prior to injection.

Warnings

For external use only. Flammable, keep away from fire or flame.

Do not use

- with electrocautery procedures
- in the eyes
- on mucous membranes
- on irritated skin.

Stop use and ask a doctor if

- irritation or redness develops.

Keep out of reach of children.

If swallowed, get medical help or contact a Poison Control center right away.

Directions

- Wipe injection site vigorously and discard.

Other information

- Store at room temperature 15 - 30°C (59 - 86°F)

Inactive ingredients:

Purified Water